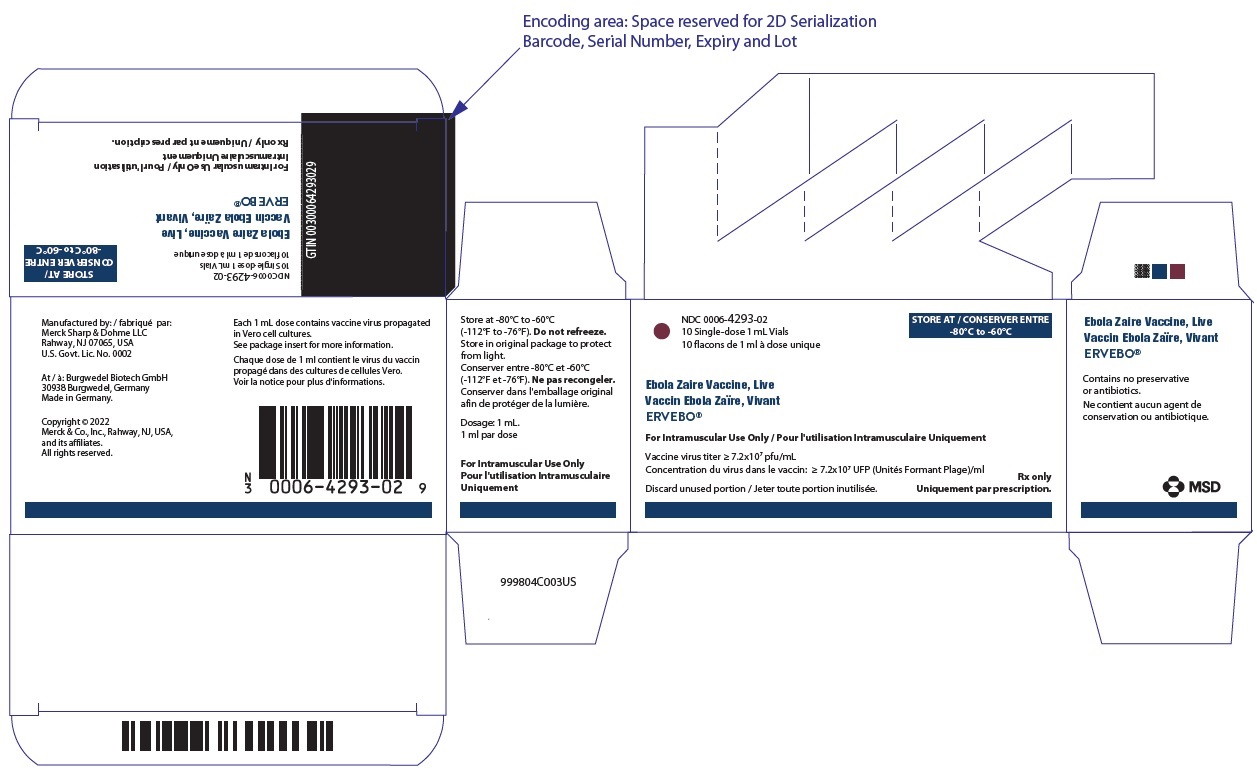 DRUG LABEL: ERVEBO
NDC: 0006-4293 | Form: INJECTION, SOLUTION
Manufacturer: Merck Sharp & Dohme LLC
Category: other | Type: VACCINE LABEL
Date: 20250131

ACTIVE INGREDIENTS: ZAIRE EBOLAVIRUS (STRAIN KIKWIT-95) ENVELOPE GLYCOPROTEIN 72000000 [PFU]/1 mL
INACTIVE INGREDIENTS: Tromethamine 0.01 mmol/1 mL; ALBUMIN HUMAN 2.5 mg/1 mL; WATER

HIGHLIGHTS OF PRESCRIBING INFORMATION

These highlights do not include all the information needed to use ERVEBO safely and effectively. See full prescribing information for ERVEBO.
ERVEBO® (Ebola Zaire Vaccine, Live) Suspension for intramuscular injection
Initial U.S. Approval: 2019

RECENT MAJOR CHANGES

Indications and Usage (1) | 07/2023

1 INDICATIONS AND USAGE

ERVEBO® is a vaccine indicated for the prevention of disease caused by Zaire ebolavirus in individuals 12 months of age and older. (1)

Limitations of Use (1.1)

- The duration of protection conferred by ERVEBO is unknown.
- ERVEBO does not protect against other species of Ebolavirus or Marburgvirus.
- Effectiveness of the vaccine when administered concurrently with antiviral medication, immune globulin (IG), and/or blood or plasma transfusions is unknown.

2 DOSAGE AND ADMINISTRATION

- Administer a single 1 mL dose of ERVEBO intramuscularly. (2.1)

3 DOSAGE FORMS AND STRENGTHS

- 1 mL suspension for injection supplied as a single-dose vial. (3)

4 CONTRAINDICATIONS

- Severe allergic reaction (e.g., anaphylaxis) to any component of ERVEBO. (4)

5 WARNINGS AND PRECAUTIONS

- Anaphylaxis has been observed following administration of ERVEBO. Appropriate medical treatment and supervision must be available in case of anaphylactic event following the administration of ERVEBO. (5.1)
- Vaccinated individuals should continue to adhere to infection control practices to prevent Zaire ebolavirus infection and transmission. (5.2)
- Vaccine virus RNA has been detected in blood, saliva, urine, and fluid from skin vesicles of vaccinated individuals; transmission of vaccine virus is a theoretical possibility. (5.4)

6 ADVERSE REACTIONS

The most commonly reported local and systemic adverse events in clinical trials were:

- Individuals 18 years of age and older: injection-site pain (70%); headache (55%); feverishness (39%); muscle pain (33%); somnolence, reduced activity, fatigue (26%); joint pain, arthralgia (19%); chills (17%); injection-site swelling (17%); decreased appetite (15%); abdominal pain (13%); injection-site redness (12%); nausea (10%); arthritis (5%); vomiting (4%), rash (4%); abnormal sweating (3%) and mouth ulceration (2%). (6.1)
- Individuals 12 months through 2 years of age: feverishness (83%); crying (31%); decreased appetite (27%); injection-site pain (26%); somnolence, reduced activity, fatigue (20%); diarrhea (19%); vomiting (17%); irritability (11%); screaming (10%); mouth ulceration (6%); chills (5%); injection-site swelling (5%); headache (4%); abdominal pain (2%); abnormal sweating (2%) and injection-site erythema (1%). (6.1)
- Individuals 3 years through 11 years of age: feverishness (65%); headache (50%); injection-site pain (40%); decreased appetite (24%); somnolence, reduced activity, fatigue (22%); abdominal pain (21%); chills (14%); myalgia (12%); vomiting (11%);dizziness (8%); nausea (8%); injection-site pruritus (7%); crying (3%); arthralgia (3%); diarrhea (3%); injection-site swelling (3%); abnormal sweating (1%); mouth ulceration (2%) and irritability (1%). (6.1)
- Individuals 12 years through 17 years of age: headache (59%); injection-site pain (52%); feverishness (48%); myalgia (30%); somnolence, reduced activity, fatigue (28%); decreased appetite (21%); chills (19%); dizziness (17%); abdominal pain (16%); arthralgia (16%); nausea (8%); abnormal sweating (5%); diarrhea (4%); vomiting (4%); injection-site pruritus (3%); injection-site swelling (3%) and mouth ulceration (2%). (6.1)

To report SUSPECTED ADVERSE REACTIONS, contact Merck Sharp & Dohme LLC at 1-877-888-4231 or VAERS at 1-800-822-7967 or www.vaers.hhs.gov.

FULL PRESCRIBING INFORMATION

1 INDICATIONS AND USAGE

ERVEBO® is indicated for the prevention of disease caused by Zaire ebolavirus in individuals 12 months of age and older.

1.1 Limitations of Use

- The duration of protection conferred by ERVEBO is unknown.
- ERVEBO does not protect against other species of Ebolavirus or Marburgvirus.
- Effectiveness of the vaccine when administered concurrently with antiviral medication, immune globulin (IG), and/or blood or plasma transfusions is unknown.

2 DOSAGE AND ADMINISTRATION

FOR INTRAMUSCULAR ADMINISTRATION ONLY.

2.1 Dosage

Administer 1 mL dose of ERVEBO.

2.2 Preparation

Thaw vial at room temperature until no visible ice is present. Do not thaw the vial in a refrigerator. Gently invert vial several times. The vaccine is a colorless to slightly brownish-yellow liquid with no particulates visible. Parenteral drug products should be inspected visually for particulate matter and discoloration prior to administration, whenever solution and container permit. If either of these conditions exist, discard the vial.

Use the vaccine immediately after thawing. If not used immediately, the vaccine may be stored for 4 hours at room temperature (up to 25°C; 77°F) protected from light. DO NOT REFREEZE [see How Supplied/Storage and Handling (16)].

Withdraw the 1 mL dose of vaccine from the vial using a sterile needle and sterile syringe.

2.3 Administration

Administer a 1 mL dose of ERVEBO intramuscularly and discard unused portion.

3 DOSAGE FORMS AND STRENGTHS

ERVEBO is a suspension for injection supplied as a 1 mL dose in single-dose vials.

4 CONTRAINDICATIONS

Do not administer ERVEBO to individuals with a history of a severe allergic reaction (e.g., anaphylaxis) to any component of the vaccine, including rice protein [see Description (11)].

5 WARNINGS AND PRECAUTIONS

5.1 Management of Acute Allergic Reactions

Among 18,616 participants vaccinated with at least one dose of ERVEBO in clinical trials, there were two reports of anaphylaxis [see Adverse Reactions (6.1)]. Monitor individuals for signs and symptoms of hypersensitivity reactions following vaccination with ERVEBO. Appropriate medical treatment and supervision must be available in case of an anaphylactic event following the administration of ERVEBO.

5.2 Limitations of Vaccine Effectiveness

Vaccination with ERVEBO may not protect all individuals. Vaccinated individuals should continue to adhere to infection control practices to prevent Zaire ebolavirus infection and transmission.

5.3 Immunocompromised Individuals

The safety and effectiveness of ERVEBO have not been assessed in immunocompromised individuals. The effectiveness of ERVEBO in immunocompromised individuals may be diminished. The risk of vaccination with ERVEBO, a live virus vaccine, in immunocompromised individuals should be weighed against the risk of disease due to Zaire ebolavirus.

5.4 Transmission

Vaccine virus RNA has been detected by RT-PCR in blood, saliva, urine, and fluid from skin vesicles of vaccinated individuals. Transmission of vaccine virus is a theoretical possibility [see Pharmacokinetics (12.3)].

6 ADVERSE REACTIONS

6.1 Clinical Trials Experience

Because clinical trials are conducted under widely varying conditions, adverse reaction rates observed in the clinical trials of a vaccine cannot be directly compared to rates in the clinical trials of another vaccine and may not reflect the rates observed in practice.

The clinical development program for ERVEBO included clinical studies conducted in North America, Europe and Africa, in which 609 participants 12 months through 17 years of age and 18,007 participants 18 years of age and older received at least one dose of ERVEBO. The number of participants vaccinated with ERVEBO in double-blind, placebo-controlled trials was 2,913 and in open-label trials was 15,703.

In Study 1 (NCT02344407), conducted in Liberia (N=1,000), participants 18 years of age and older were randomized 1:1 to receive ERVEBO or saline placebo. Participants were assessed at Week 1 and Month 1 postvaccination for solicited local and systemic reactions. In a subset of participants (n=201), joint symptoms and signs were also solicited during a Week 2 visit. Memory aids were not used and postvaccination temperatures were measured only at study visits. Unsolicited adverse events were collected through Month 1 postvaccination. The median age of participants was 29 years, 63.6% were male and 100% were Black. Serious adverse events were monitored through 1-year postvaccination.

In Study 2 (NCT02503202), conducted in the United States, Canada and Spain (N=1,197), participants 18 through 65 years of age were randomized to receive ERVEBO (n=1,061) or saline placebo (n=133). Participants used a memory aid to record solicited local reactions from Days 1 to 5 postvaccination, and daily temperature measurements and solicited joint and skin events from Days 1 to 42 postvaccination. Unsolicited adverse reactions were collected through Day 42 postvaccination. The median age of participants was 42 years; 46.8% were male; 67.9% were White, 29.2% were Black or African American, 1.4% were Multi-racial, 0.8% were Asian, 0.4% were American Indian or Alaska Native, and 0.3% were Native Hawaiian or Pacific Islander; 14.5% were Hispanic or Latino. Serious adverse events were monitored through 6 months postvaccination, and a subset of participants (n=511) were monitored through 24 months postvaccination.

In Study 3 (Pan African Clinical Trials Registry, PACTR201503001057193), an open-label cluster-randomized study conducted in the Republic of Guinea, 5,643 participants 18 years of age and older received a dose of ERVEBO. The median age of vaccinated participants was 37 years, 68% were male and 100% were Black. Serious adverse events were monitored through 84 days postvaccination.

In Study 4 (NCT02378753), a randomized open-label study conducted in Sierra Leone, 7,998 participants 18 years of age and older received a dose of ERVEBO. The median age of participants was 31 years, 63% were male; 99.8% were Black and 0.2% collectively were Multi-racial, Asian or White. Serious adverse events were monitored through 180 days postvaccination.

In Study 5 (Pan African Clinical Trials Registry, PACTR201503001057193), an open-label safety and immunogenicity trial conducted in vaccinated frontline workers in the Republic of Guinea, implemented as Part B of Study 3, 2,016 participants 18 years of age and older received a dose of ERVEBO. The median age of vaccinated participants was 30 years, 75% were male and 100% were Black. Serious adverse events were monitored through 85 days postvaccination.

Study 6 (NCT02876328) is an ongoing, double-blind, randomized placebo-controlled study conducted in Liberia, Sierra Leone, Mali and the Republic of Guinea in which participants received ERVEBO or an investigational Ebola vaccine or placebo. A total of 155 participants 12 months through 2 years of age, 515 participants 3 through 11 years of age, 328 participants 12 through 17 years of age and 1,004 participants 18 years of age and older received a single dose of ERVEBO and saline placebo administered 56 days apart, or two doses of ERVEBO administered 56 days apart (not an approved dosing regimen), or two doses of saline placebo. Memory aids were not used. Participants were observed at the study site for 30 minutes after vaccination. Participants were assessed for solicited local and systemic reactions at study visits on day of vaccination (Day 0), Day 7, Day 14 and Day 28 after each vaccination. Postvaccination temperatures were obtained from participants 12 months through 17 years of age at daily contacts on Days 1 through 7, and on Day 14 and Day 28 after the first vaccination and Days 1 through 7 after the second vaccination. Postvaccination temperatures were obtained from participants 18 years of age and older at study visits. At each study visit, participants or their caregivers were queried about the occurrence of unsolicited adverse events. In this study, Grade 3 events were defined as symptoms causing inability to perform usual social and functional activities. Grade 4 events were defined as symptoms causing inability to perform basic self-care functions or medical or operative intervention indicated to prevent permanent impairment, persistent disability, or death. The median age of participants 18 years of age and older was 27 years and 54.6% were male, and the median age of participants 12 months through 17 years of age was 8 years and 54.7% were male. Serious adverse events were monitored through 12 months postvaccination.

Eight additional studies (NCT02269423, NCT02280408, NCT02374385, NCT02314923, NCT02287480, NCT02283099, NCT02296983) contributed to the assessment of serious adverse reactions.

Adverse Reactions in Participants 18 Years of Age and Older

Table 1 presents the proportion of participants reporting solicited adverse reactions in Study 1.

Table 1: Percentage of Participants 18 Years of Age and Older with Solicited Local and Systemic Adverse Reactions After Vaccination (Study 1)
 | ERVEBO % | PLACEBO %
Injection-site reactions [Adverse reactions were solicited at 30 minutes, Week 1 and Month 1 postvaccination.] | N=500 | N=500
Injection site pain | 34.0 | 11.2
Local reactions (redness/swelling) | 1.8 | 0.8
Systemic adverse reactions [Adverse reactions were solicited at Week 1 and Month 1 postvaccination.] | N=498 | N=499
Headache | 36.9 | 23.2
Feverishness | 34.3 | 14.8
Muscle pain | 32.5 | 22.8
Fatigue | 18.5 | 13.4
Nausea | 8.0 | 4.4
Joint pain/tenderness | 7.0 | 5.8
Rash | 3.6 | 3.2
Abnormal sweating | 3.2 | 2.6
Arthropathy (joint redness/warmth) [In a subset of participants (n=201), joint symptoms and signs were also solicited during a Week 2 visit.] | 0.6 | 0.2
Joint swelling | 0.4 | 0.4
Joint stiffness | 0.4 | 0.2

In Study 1, 56.4% of participants reported at least one of the solicited systemic adverse reactions listed in Table 1 within seven days after vaccination. With the exception of one participant who reported events of moderate intensity (causing greater than minimal interference with daily activity), all others reported events of mild intensity (causing no or minimal interference with daily activity).

Table 2 presents the proportion of participants 18 years of age and older reporting solicited adverse reactions in Study 2.

Table 2: Percentage of Participants 18 Years of Age and Older with Solicited Local and Systemic Adverse Reactions After Vaccination (Study 2)
 | ERVEBO % | PLACEBO %
Injection-site reactions [Adverse reactions were solicited Days 1 to 5 postvaccination.] | N=1051 | N=133
Injection-site pain | 69.5 | 12.8
Injection-site swelling | 16.5 | 3.0
Injection-site redness | 11.9 | 1.5
Systemic adverse reactions [Adverse reactions were solicited Day 1 through Day 42 postvaccination.] | N=1051 | N=133
Joint pain | 17.9 | 3.0
Arthritis (composite term) [Arthritis is a composite term that includes preferred terms of arthritis, monoarthritis, polyarthritis, osteoarthritis, joint swelling, or joint effusion.] | 4.7 | 0.0
Rash (composite term) [Rash is a composite term that includes petechiae, purpura, rash, rash generalized, rash macular, rash papular and rash vesicular.] | 3.8 | 1.5
Vesicular lesions [Vesicular lesions include events reported as rash vesicular in the rash composite term and reported as blister.] | 1.5 | 0.0

In Study 2, 29 participants (2.8%) reported injection-site pain of severe intensity. Severe arthritis (arthritis and joint swelling) was reported by 8 participants (0.8%) and severe arthralgia was reported by 14 participants (1.3%). In this study, severe events were defined as incapacitating with inability to work or do usual activity.

Table 3 presents the proportion of participants 18 years of age and older reporting solicited adverse reactions in Study 6 within 28 days following administration of the first dose.

Table 3: Percentage of Participants 18 Years of Age and Older with Solicited Local and Systemic Adverse Reactions within 28 Days After the First Dose (Study 6)
 | ERVEBO % | PLACEBO %
Injection-site reactions [Adverse reactions were solicited postvaccination on day of vaccination (Day 0), Day 7, Day 14 and Day 28.] | N=592 | N=412
Injection-site pain | 21.5 | 4.1
Injection-site swelling | 3.7 | 2.9
Injection-site erythema | 1.4 | 2.4
Systemic adverse reactions | N=592 | N=412
Headache | 55.1 | 43.4
Feverishness [Feverishness was not defined by a specific temperature measurement.] | 39.2 | 22.8
Myalgia | 29.6 | 15.8
Somnolence [Includes: somnolence, reduced activity and fatigue.] | 25.5 | 13.6
Arthralgia | 18.6 | 10.7
Chills | 16.7 | 8.5
Decreased appetite | 15.2 | 9.5
Abdominal pain | 13.0 | 11.2
Nausea | 9.5 | 6.3
Vomiting | 4.4 | 1.2
Mouth ulceration | 2.2 | 0.5
Abnormal sweating | 1.4 | 1.0
Joint swelling | 0.7 | 0.0

Most (>98%) reactions presented in Table 3 were mild to moderate in intensity.

Adverse Reactions in Participants 12 Months through 17 Years of Age

Table 4 presents the proportion of participants reporting solicited adverse reactions within 28 days following administration of the first dose in Study 6.

Table 4: Percentage of Participants 12 Months through 17 Years of Age with Solicited Local and Systemic Adverse Reactions within 28 Days After First Dose (Study 6)
 | 12 Months through 2 Years of Age |  | 3 Years through 11 Years of Age |  | 12 Years through 17 Years of Age
 | ERVEBO % N=95 | PLACEBO % N=60 | ERVEBO % N=310 | PLACEBO % N=205 | ERVEBO % N=203 | PLACEBO % N=123
Injection-site reactions [Adverse reactions were solicited postvaccination on day of vaccination (Day 0), Day 1 through Day 7, Day 14 and Day 28.]
Injection-site pain | 26.3 | 8.3 | 39.4 | 8.8 | 52.2 | 17.1
Injection-site swelling | 5.3 | 3.3 | 2.6 | 2.0 | 2.5 | 2.4
Injection-site erythema | 1.1 | 3.3 | 0.3 | 0.5 | 0.5 | 0
Injection-site pruritus | N/A | N/A | 6.5 | 0 | 2.5 | 0.8
Systemic adverse reactions
Feverishness [Feverishness was not defined by a specific temperature measurement.] | 83.2 | 66.7 | 64.8 | 37.1 | 48.3 | 27.6
Crying | 30.5 | 6.7 | 3.2 | 2.4 | N/A | N/A
Decreased appetite | 27.4 | 15.0 | 23.9 | 13.2 | 20.7 | 14.6
Somnolence [Includes: somnolence, reduced activity and fatigue.] | 20.0 | 8.3 | 21.6 | 9.8 | 28.1 | 19.5
Diarrhea | 18.9 | 16.7 | 2.9 | 4.4 | 3.9 | 4.1
Vomiting | 16.8 | 10.0 | 11.0 | 8.8 | 3.9 | 3.3
Irritability | 10.5 | 1.7 | 1.0 | 0.0 | N/A | N/A
Screaming | 9.5 | 1.7 | 0.6 | 0.5 | N/A | N/A
Mouth ulceration | 6.3 | 1.7 | 1.9 | 0.5 | 1.5 | 0
Chills | 5.3 | 3.3 | 14.2 | 10.7 | 19.2 | 16.3
Headache | 4.2 | 5.0 | 49.7 | 34.6 | 59.1 | 39.0
Abdominal pain | 2.1 | 3.3 | 21.0 | 14.1 | 15.8 | 13.0
Abnormal sweating | 2.1 | 3.3 | 1.3 | 2.0 | 4.9 | 0.8
Arthralgia | N/A | N/A | 3.2 | 2.0 | 15.8 | 8.1
Dizziness | N/A | N/A | 8.4 | 4.4 | 16.7 | 11.4
Myalgia | N/A | N/A | 11.6 | 3.9 | 29.6 | 9.8
Nausea | 0 | 1.7 | 8.4 | 3.4 | 8.4 | 8.1
N/A: Not applicable because not assessed in this age group.

Most (>98%) reactions presented in Table 4 were mild to moderate in intensity.

Table 5 presents the proportion of participants 12 months through 17 years of age reporting fever within 7 days following administration of the first dose in Study 6.

Table 5: Percentage of Participants 12 Months through 17 Years of Age with Fever Within 7 Days After the First Dose (Study 6) [The use of antipyretic medication within 48 hours postvaccination was reported in 67% and 43% of participants 12 months through 2 years of age, 58% and 37% of participants 3 through 11 years of age, and 52% and 27% of participants 12 through 17 years of age for ERVEBO and placebo, respectively.]
Age | Maximum Temperature (Temporal) | ERVEBO % | PLACEBO %
12 Months through 2 Years of Age | ≥38.0°C to ≤38.4°C >38.4°C to ≤38.9°C >38.9°C to ≤40.0°C >40.0°C | N=95 3.2 3.2 0.0 0.0 | N=60 1.7 1.7 1.7 0.0
3 Years through 11 Years of Age | ≥38.0°C to ≤38.4°C >38.4°C to ≤38.9°C >38.9°C to ≤40.0°C >40.0°C | N=310 4.2 1.0 1.3 0.0 | N=205 0.5 1.5 0.0 0.0
12 Years through 17 Years of Age | ≥38.0°C to ≤38.4°C >38.4°C to ≤38.9°C >38.9°C to ≤40.0°C >40.0°C | N=203 2.5 2.5 2.5 0.0 | N=122 0.8 0.8 0.8 0.0

Unsolicited Adverse Reactions

In Study 2, the unsolicited adverse reaction of chills was reported in 7.3% of ERVEBO recipients compared to 0% of placebo recipients. Paresthesia was reported by 1.4% of ERVEBO recipients compared to 0% of those who received placebo in this study.

Arthralgia and Arthritis

In an analysis across blinded, placebo-controlled studies (excluding Study 6), arthralgia was reported to occur in 7% to 40% of vaccine recipients. Arthralgia was generally reported in the first few days following vaccination, was of mild to moderate intensity, and resolved within one week after onset. Severe arthralgia, defined as preventing daily activity, was reported in up to 3% of participants.

In an analysis across blinded, placebo-controlled studies (excluding Study 6) in which participants received ERVEBO or a lower dose formulation, arthritis (including events of arthritis, joint effusion, joint swelling, osteoarthritis, monoarthritis or polyarthritis) was reported to occur in 0% to 24% of participants, with all but one study reporting arthritis in <5% of participants. Most occurrences of arthritis were reported within the first few weeks following vaccination, were of mild to moderate intensity, and resolved within several weeks after onset. In one study conducted in Switzerland (NCT02287480), 102 participants received ERVEBO or a lower dose formulation. In this study, arthritis was reported to occur in 24% of participants and severe arthritis, defined as preventing daily activity, in 12% of participants. Joint effusion samples were obtained from three participants and all three tested positive for vaccine virus RNA by RT-PCR. Of all 24 participants with arthritis in this study, six participants reported recurrent or prolonged joint symptoms lasting up to 2 years following vaccination, the longest follow-up period.

Rash

In an analysis across blinded, placebo-controlled studies (excluding Study 6), rash was reported to occur after administration of ERVEBO, with all but one study reporting rash in <9% of participants. In one study (NCT02287480), rash was reported to occur in 25% (n=4) of ERVEBO recipients and 7.7% (n=1) of placebo recipients. In this study, cutaneous vasculitis was reported in two participants who received a lower dose formulation, neither of whom had evidence of systemic vasculitis. Vesicular fluid and skin biopsy samples taken from some participants reporting rash have tested positive for vaccine virus RNA by RT-PCR.

Decreases in Lymphocytes and Neutrophils

White blood cell counts were assessed in 697 participants who received ERVEBO. Decreases in lymphocytes were reported in up to 85% of participants and decreases in neutrophils were reported in up to 43% of participants. No associated infections were reported.

Serious Adverse Reactions

In 18,616 ERVEBO recipients, two serious adverse reactions of pyrexia were reported as vaccine-related. In addition, two serious adverse reactions of anaphylaxis were reported as vaccine-related. These serious adverse reactions occurred in participants 18 years of age and older, and none were fatal.

7 DRUG INTERACTIONS

7.1 Interference with Laboratory Tests

Following vaccination with ERVEBO, individuals may test positive for anti-Ebola glycoprotein (GP) antibody and/or Ebola GP nucleic acid or antigens. GP-based testing may have limited diagnostic value during the period of vaccine viremia, in the presence of vaccine-derived Ebola GP, and following antibody response to the vaccine [see Pharmacokinetics (12.3)].

8 USE IN SPECIFIC POPULATIONS

8.1 Pregnancy

Risk Summary

All pregnancies have a risk of birth defect, loss, or other adverse outcomes. In the U.S. general population, the estimated background risk of major birth defects and miscarriage in clinically recognized pregnancies is 2% to 4% and 15% to 20%, respectively.

There are no adequate and well-controlled studies of ERVEBO in pregnant women, and human data available from clinical trials with ERVEBO are insufficient to establish the presence or absence of vaccine-associated risk during pregnancy.

The decision to vaccinate a woman who is pregnant should consider the woman's risk of exposure to Zaire ebolavirus.

A developmental toxicity study has been performed in female rats administered a single human dose of ERVEBO on four occasions; twice prior to mating, once during gestation and once during lactation. This study revealed no evidence of harm to the fetus due to ERVEBO [see Animal Data below].

Clinical Considerations

Disease-associated Maternal and/or Embryo/Fetal Risk

Fetal and neonatal outcomes are universally poor among pregnant women infected with Zaire ebolavirus. The majority of such pregnancies end in miscarriage or stillbirth. In pregnancies where live birth does occur, neonates generally do not survive.

Fetal/Neonatal Adverse Reactions

The potential for transmission of the vaccine virus from mother to the fetus/neonate is unknown.

Data

Animal Data

In a developmental toxicity study, female rats received a single human dose of ERVEBO by intramuscular injection on four occasions: 28 days and 7 days prior to mating, gestation day 6 and lactation day 7. No adverse effects on pre-weaning development up to post-natal day 21 were observed. There were no vaccine-related fetal malformations or variations observed.

8.2 Lactation

Risk Summary

Human data are not available to assess the impact of ERVEBO on milk production, its presence in breast milk, or its effects on the breastfed child. The developmental and health benefits of breastfeeding should be considered along with the mother's clinical need for ERVEBO and any potential adverse effects on the breastfed child from ERVEBO or from the underlying maternal condition. For preventive vaccines, the underlying condition is susceptibility to disease prevented by the vaccine.

8.4 Pediatric Use

The safety and effectiveness of ERVEBO in individuals 12 months through 17 years of age have been established [see Adverse Reactions (6.1) and Clinical Studies (14.2)]. The safety and effectiveness of ERVEBO in individuals younger than 12 months of age have not been established.

8.5 Geriatric Use

Across the clinical development program, the total number of participants ≥65 years of age who received at least one dose of ERVEBO was 554.

Clinical studies of ERVEBO did not include sufficient numbers of participants 65 years of age and older to determine whether they respond differently from younger participants.

11 DESCRIPTION

ERVEBO (Ebola Zaire Vaccine, Live) is a sterile suspension for intramuscular injection. ERVEBO is a live recombinant viral vaccine consisting of a vesicular stomatitis virus (VSV) backbone deleted for the VSV envelope glycoprotein and substituted with the envelope glycoprotein of the Zaire ebolavirus (Kikwit 1995 strain). The vaccine virus is grown in serum-free Vero cell cultures. The virus is harvested from the cell culture medium, purified, formulated with stabilizer solution, filled into vials and stored frozen. When thawed, ERVEBO is a colorless to slightly brownish-yellow liquid with no particulates visible.

Each 1 mL dose of ERVEBO contains a minimum of 72 million plaque forming units (pfu) of vaccine virus in a stabilizer solution containing 10 mM Tromethamine (Tris) and 2.5 mg/mL rice-derived recombinant human serum albumin. Each 1 mL dose may contain residual amounts of host cell DNA (≤10 ng) and benzonase (≤15 ng). The vaccine may contain trace amounts of rice protein. The product contains no preservatives.

The vaccine vial stopper is not made with natural rubber latex.

12 CLINICAL PHARMACOLOGY

12.1 Mechanism of Action

Immunization with ERVEBO results in an immune response and protection from disease caused by Zaire ebolavirus. The relative contributions of innate, humoral and cell-mediated immunity to protection from Zaire ebolavirus are unknown.

12.3 Pharmacokinetics

Viremia

Vaccine viremia was evaluated in 186 participants enrolled in seven clinical studies who were vaccinated with ERVEBO. Vaccine virus RNA was detected by RT-PCR in the plasma of most participants from Day 1 to Day 7 postvaccination with one participant having a positive plasma RT-PCR result 14 days after vaccination.

Shedding

Shedding of vaccine virus into the urine or saliva was evaluated in 359 participants enrolled in 8 clinical studies who were vaccinated with ERVEBO or lower dose formulations. Vaccine virus RNA was detected by RT-PCR in the urine or saliva of some participants at timepoints ranging from Day 1 through Day 14 postvaccination. In the 3 studies that assessed shedding at Day 28, no samples tested positive. In Study 6, 31.7% (19/60) of participants 12 months through 17 years of age enrolled in a substudy shed vaccine virus in saliva following vaccination. Viral shedding was greatest on Day 7 and declined thereafter, with no shedding detected after Day 28.

Vaccine virus RNA was detected by RT-PCR in vesicular fluid samples from some participants. In one participant, a sample collected 20 days after vaccination tested positive for vaccine virus RNA by RT-PCR.

13 NONCLINICAL TOXICOLOGY

13.1 Carcinogenesis, Mutagenesis, Impairment of Fertility

ERVEBO has not been evaluated for the potential to cause carcinogenicity, genotoxicity or impairment of male fertility. ERVEBO administered to female rats had no effects on fertility [see Use in Specific Populations (8.1)].

14 CLINICAL STUDIES

14.1 Clinical Efficacy

Clinical efficacy of ERVEBO was assessed in Study 3.

Study 3 (Ring vaccination study) was an open-label, randomized cluster (ring) vaccination study conducted in the Republic of Guinea during the 2014 outbreak. Each cluster was composed of contacts and contacts of contacts of individuals with laboratory-confirmed Ebola virus disease (EVD). Clusters were randomized to receive either an "immediate" vaccination or a 21-day "delayed" vaccination. In the primary efficacy analysis, 3,537 participants ≥18 years of age were considered contacts and contacts of contacts of an index case with laboratory-confirmed EVD. Of these, 2,108 were included in 51 immediate vaccination clusters, and 1,429 were included in 46 delayed vaccination clusters.

The median age of participants in the primary efficacy analysis was 40 years. The majority were male, comprising 70.4% and 70.3% in the randomized immediate and delayed clusters, respectively.

In the primary efficacy analysis, the number of cases of laboratory-confirmed EVD in participants vaccinated in immediate vaccination clusters was compared to the number of cases in participants in delayed vaccination clusters. Cases of EVD that occurred between Day 10 and Day 31 post-randomization of the cluster were included in the analysis. Vaccine efficacy was 100% (95% CI: 63.5% to 100%); no cases of confirmed EVD were observed in the immediate vaccination clusters, and 10 confirmed cases of EVD were observed in a total of 4 delayed vaccination clusters between Day 10 and Day 31 post-randomization.

14.2 Clinical Immunogenicity

A measure of the immune response that confers protection against EVD is unknown.

Clinical Immunogenicity in Individuals 18 Years of Age and Older Across Geographic Areas

Four studies assessed antibody responses to ERVEBO in participants 18 years of age and older (Study 1, Study 2, Study 4 and Study 5), including 477 participants in Liberia, 506 participants in Sierra Leone, 915 participants in the US, Canada, and Spain (n=865 US participants) and 1,217 participants in the Republic of Guinea. Zaire ebolavirus (Kikwit) GP-specific immunoglobulin G (IgG) was detected by enzyme linked immunosorbent assay (GP-ELISA). Vaccine virus neutralizing antibody was detected by a plaque reduction neutralization test (PRNT).

Antibody responses among participants in the study conducted in the US, Canada, and Spain (Study 2) were similar to those among participants in the studies conducted in Liberia (Study 1), Sierra Leone (Study 4) and the Republic of Guinea (Study 5).

Clinical Immunogenicity in Individuals 12 Months through 17 Years of Age

A fifth study (Study 6) conducted in Liberia, Sierra Leone, Mali and the Republic of Guinea assessed antibody geometric mean titers (GMT) to ERVEBO in 386 participants 12 months through 17 years of age compared to 386 participants 18 years of age and older. Zaire ebolavirus (Kikwit) GP-specific immunoglobulin G (IgG) was detected by enzyme linked immunosorbent assay (GP-ELISA). GMTs at Day 28 after vaccination with ERVEBO in participants 12 months through 17 years of age were non-inferior to those in participants 18 years of age and older (see Table 6).

Table 6: Non-inferiority Analysis of Pooled Geometric Mean Titers at Day 28 for the GP-ELISA (Study 6)
Individuals 12 Months through 17 Years of Age n=499 | Individuals 18 Years of Age and Older n=519 | GMT ratio [GMT (individuals 12 months through 17 years of age) / GMT (individuals 18 years of age and older); Non-inferiority is declared if the lower bound of the 2-sided 95% CI for the GMT ratio is greater than 0.5.] (95% CI)
GMT (95% CI) | GMT (95% CI) | 1.42 (1.24, 1.62)
1748.8 (1585.6, 1928.7) | 1234.4 (1132.5, 1345.4) | 1.42 (1.24, 1.62)
The Per-Protocol Immunogenicity Population was the primary population for the immunogenicity analyses in Study 6 and includes all vaccinated participants with serology data who were compliant with the protocol and had a serum sample collected within an acceptable day range.
n=Number of participants contributing to the analysis.
CI=Confidence interval; GMT=geometric mean titer; GP-ELISA=glycoprotein enzyme-linked immunosorbent assay.
Study 6 used gamma irradiation of specimens to reduce risk of wild-type Ebola virus infection of laboratory workers.

16 HOW SUPPLIED/STORAGE AND HANDLING

Carton of ten 1 mL single-dose vials. NDC 0006-4293-02

STORAGE AND HANDLING

Store frozen at -80°C to -60°C (-112°F to -76°F). Store in the original carton to protect from light.

Do not thaw the vial in a refrigerator. Thaw the vial at room temperature until no visible ice is present. Use the vaccine immediately after thawing. If not used immediately, a thawed vial can be stored refrigerated at 2°C to 8°C (35.6°F to 46.4°F) for a total time of no more than 2 weeks and at room temperature (up to 25°C; 77°F) for a total time of no more than 4 hours. Protect from light. Do not re-freeze thawed vaccine.

17 PATIENT COUNSELING INFORMATION

Advise the vaccine recipients, parents or guardians to read the FDA-approved patient labeling (Patient Information).

Advise vaccine recipients, parents or guardians of the following:

- ERVEBO has not been demonstrated to provide protection against disease caused by viruses other than Zaire ebolavirus. After vaccination with ERVEBO, individuals at risk should continue to protect themselves from exposure to Zaire ebolavirus.
- ERVEBO may not protect all vaccinated individuals.
- Transmission of vaccine virus is a theoretical possibility. Vaccine virus RNA has been detected in blood, saliva, or urine for up to 14 days after vaccination. The duration of shedding is not known; however, samples taken 28 days after vaccination tested negative. Vaccine virus RNA has been detected in fluid from skin vesicles that appeared after vaccination.

Instruct vaccine recipients, parents or guardians to:

- Report any adverse reactions to their health care provider.
- Seek immediate medical attention if any signs or symptoms of a hypersensitivity reaction occur after vaccination [see Contraindications (4)].

Manufactured by: Merck Sharp & Dohme LLC
Rahway, NJ 07065, USA

For patent information: www.msd.com/research/patent

Copyright © 2019-2023 Merck & Co., Inc., Rahway, NJ, USA, and its affiliates.
All rights reserved.

uspi-v920-i-2307r003

Patient Information about
ERVEBO® (pronounced "er-VEE-boh")
(Ebola Zaire Vaccine, Live)

Before you or your child get ERVEBO®, read this document and be sure you understand all of the information. Keep this document. You may need to read it again. If you have questions or side effects, ask the health care provider. This information does not take the place of talking about ERVEBO with the health care provider.

You or your child may be advised to get this vaccine in an emergency situation.

What is ERVEBO?

- ERVEBO is a vaccine to prevent disease caused by Zaire ebolavirus in individuals who are 12 months of age and older.
- This vaccine is given to help protect you or your child from getting Ebola virus disease caused by one type of Ebola virus (Zaire ebolavirus). This vaccine will not protect against disease caused by other types of Ebola virus.
- You or your child cannot get Ebola virus disease from ERVEBO.
- After getting ERVEBO, you or your child should continue to protect against exposure to Ebola virus.
- ERVEBO might not protect everyone who gets the vaccine.

What should I tell the health care provider before getting ERVEBO?

You should tell the health care provider if you or your child:

- have ever had an allergic reaction to a vaccine or medicine
- have ever had an allergic reaction to ERVEBO, rice protein or any of the ingredients in this vaccine
- are pregnant or breastfeeding
- think you or your child may be pregnant or are planning to have a baby
- have a weakened immune system or take medicines or treatments that might weaken the immune system
- have close contact with anyone who has a weakened immune system

How will I get ERVEBO?

ERVEBO is given as an injection.

What are the side effects of ERVEBO?

Serious allergic reactions have been observed after administration of ERVEBO. Tell the health care provider promptly about any unusual or severe symptoms that develop after getting this vaccine. Get medical care right away if you or your child have signs of an allergic reaction, which may include:

- wheezing or trouble breathing
- swelling of the face, lips, tongue, or other parts of the body
- generalized itching, redness, flushing or itchy bumps on the skin

Other side effects in individuals 18 years of age and older:

- Pain, swelling, or redness at the injection site
- Fever
- Feeling tired
- Joint pain
- Muscle aches
- Headache
- Stomach pain

- Chills
- Abnormal sweating
- Nausea
- Skin rash (including blisters)
- Joint swelling
- Eating less than usual
- Mouth sores
- Vomiting

Certain white blood cell counts can become lower than normal after vaccination but are not associated with illness and go back to normal.

Most side effects go away within a few days. Joint pain and swelling may last for weeks, months, or years in some people. In some people, joint pain and swelling may come back after initially going away.

Side effects in individuals 12 months through 17 years of age:

- Pain, itching, swelling, or redness at the injection site
- Fever
- Headache
- Feeling tired
- Eating less than usual
- Muscle aches
- Crying
- Feeling dizzy
- Mouth sore

- Abdominal pain
- Vomiting
- Chills
- Diarrhea
- Joint pain
- Irritability
- Screaming
- Abnormal sweating
- Nausea

If you or your child have any side effect that bothers you or your child or does not go away, tell the doctor, pharmacist or nurse.
There may be other side effects that are not listed here.
Talk to the doctor, pharmacist or nurse with questions or concerns about possible side effects.
You may also report any side effects to Merck Sharp & Dohme LLC at 1-877-888-4231 or directly to Vaccine Adverse Event Reporting System (VAERS). The VAERS toll-free number is 1-800-822-7967 or report online to www.vaers.hhs.gov .

Other information

- ERVEBO may cause you or your child to have a positive test for Ebola, even if you or your child don't have the disease. Tell the health care provider that you or your child received ERVEBO. The health care provider might need to do a different test.

What is in ERVEBO?

Active ingredient: live Vesicular Stomatitis Virus in which the surface protein has been replaced with that of Zaire ebolavirus.

Inactive ingredients: recombinant human serum albumin, tromethamine (Tris) buffer.

This vaccine contains a trace amount of rice protein.

What if I have other questions?

- To learn more about ERVEBO, talk to the health care provider.
- Keep this information about ERVEBO. You might want to look at it again.

Manufactured by: Merck Sharp & Dohme LLC
Rahway, NJ 07065, USA

For patent information: www.msd.com/research/patent

Copyright © 2019-2025 Merck & Co., Inc., Rahway, NJ, USA, and its affiliates.

All rights reserved.

usppi-v920-i-2501r003

This Patient Information has been approved by the U.S. Food and Drug Administration.

Revised: 01/2025

PRINCIPAL DISPLAY PANEL

NDC 0006-4293-02
10 Single-dose 1 mL Vials
10 flacons de 1 ml à dose unique

STORE AT / CONSERVER ENTRE
-80°C to -60°C

Ebola Zaire Vaccine, Live
Vaccin Ebola Zaïre, Vivant
ERVEBO®

For Intramuscular Use Only / Pour l'utilisation Intramusculaire Uniquement

Vaccine virus titer ≥ 7.2x10^7 pfu/mL
Concentration du virus dans le vaccin: ≥ 7.2x10^7 UFP (Unités Formant Plage)/ml

Discard unused portion / Jeter toute portion inutilisée.

Rx only
Uniquement par prescription.